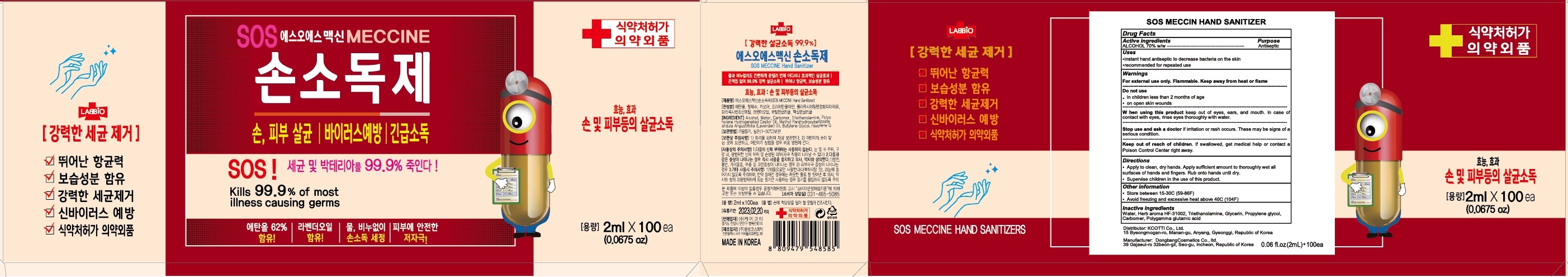 DRUG LABEL: SOS MECCIN HAND SANITIZER
NDC: 77749-010 | Form: GEL
Manufacturer: KCOTTI.Co,. LTD
Category: otc | Type: HUMAN OTC DRUG LABEL
Date: 20200520

ACTIVE INGREDIENTS: ALCOHOL 70 g/100 mL
INACTIVE INGREDIENTS: Water; TROLAMINE; Glycerin; Propylene glycol; CARBOMER HOMOPOLYMER, UNSPECIFIED TYPE

ACTIVE INGREDIENT

ALCOHOL 70% w/w

INACTIVE INGREDIENT

Water, Herb aroma HF-31002, Triethanolamine, Glycerin, Propylene glycol, Carbomer, Polygamma glutamic acid

PURPOSE

Antiseptic

WARNINGS

For external use only. Flammable. Keep away from heat or flame
--------------------------------------------------------------------------------------------------------
Do not use
• in children less than 2 months of age
• on open skin wounds
--------------------------------------------------------------------------------------------------------
When using this product keep out of eyes, ears, and mouth. In case of contact with eyes, rinse eyes thoroughly with water.
--------------------------------------------------------------------------------------------------------
Stop use and ask a doctor if irritation or rash occurs. These may be signs of a serious condition.

KEEP OUT OF REACH OF CHILDREN

If swallowed, get medical help or contact a Poison Control Center right away.

Uses

•instant hand antiseptic to decrease bacteria on the skin
•recommended for repeated use

Directions

• Apply to clean, dry hands. Apply sufficient amount to thoroughly wet all surfaces of hands and fingers. Rub onto hands until dry.
• Supervise children in the use of this product.

Other Information

• Store between 15-30C (59-86F)
• Avoid freezing and excessive heat above 40C (104F)